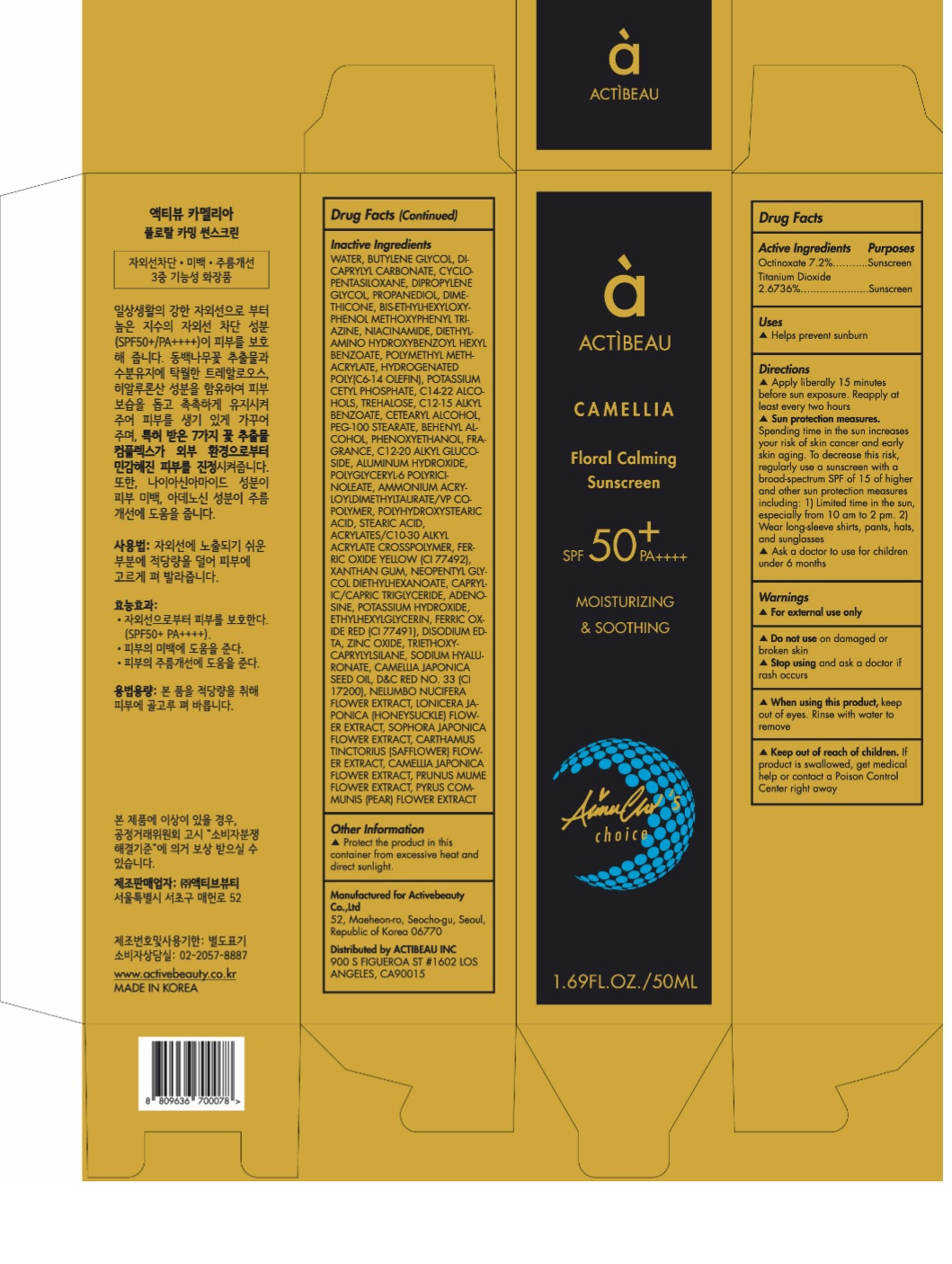 DRUG LABEL: ACTIBEAU Camellia Floral Calming Sunscreen
NDC: 73016-004 | Form: CREAM
Manufacturer: ACTIVEBEUTY CO.,LTD
Category: otc | Type: HUMAN OTC DRUG LABEL
Date: 20190403

ACTIVE INGREDIENTS: OCTINOXATE 72 mg/1 mL; TITANIUM DIOXIDE 26.736 mg/1 mL
INACTIVE INGREDIENTS: WATER; BUTYLENE GLYCOL; DICAPRYLYL CARBONATE; CYCLOMETHICONE 5; DIPROPYLENE GLYCOL; PROPANEDIOL; DIMETHICONE; BEMOTRIZINOL; NIACINAMIDE; DIETHYLAMINO HYDROXYBENZOYL HEXYL BENZOATE; POLY(METHYL METHACRYLATE; 450000 MW); HYDROGENATED POLY(C6-14 OLEFIN; 2 CST); POTASSIUM CETYL PHOSPHATE; C14-22 ALCOHOLS; TREHALOSE; ALKYL (C12-15) BENZOATE; CETOSTEARYL ALCOHOL; PEG-100 STEARATE; DOCOSANOL; PHENOXYETHANOL; C12-20 ALKYL GLUCOSIDE; ALUMINUM HYDROXIDE; AMMONIUM ACRYLOYLDIMETHYLTAURATE/VP COPOLYMER; POLYHYDROXYSTEARIC ACID (2300 MW); STEARIC ACID; CARBOMER INTERPOLYMER TYPE A (ALLYL SUCROSE CROSSLINKED); FERRIC OXIDE YELLOW; XANTHAN GUM; NEOPENTYL GLYCOL DIETHYLHEXANOATE; MEDIUM-CHAIN TRIGLYCERIDES; ADENOSINE; POTASSIUM HYDROXIDE; ETHYLHEXYLGLYCERIN; FERRIC OXIDE RED; EDETATE DISODIUM ANHYDROUS; ZINC OXIDE; TRIETHOXYCAPRYLYLSILANE; HYALURONATE SODIUM; CAMELLIA JAPONICA SEED OIL; D&C RED NO. 33; NELUMBO NUCIFERA FLOWER; LONICERA JAPONICA FLOWER; STYPHNOLOBIUM JAPONICUM FLOWER; SAFFLOWER; CAMELLIA JAPONICA FLOWER; PRUNUS MUME FLOWER; PYRUS COMMUNIS FLOWER

73016-004

ACTIVE INGREDIENT

Octinoxate 7.2%
Titanium Dioxide 4.8184%

PURPOSE

Sunscreen

INDICATIONS AND USAGE

Helps prevent sunburn

DOSAGE AND ADMINISTRATION

Apply liberally 15 minutes before sun exposure. Reapply at least every two hours

WARNINGS

For external use only.
Do not use on damaged or broken skin.
When using this product, keep out of eyes. Rinse with water to remove.
Stop using and ask a doctor if rash occurs.

KEEP OUT OF REACH OF CHILDREN

Keep out of reach of the children. If product is swallowed, get medical help or contact a poison control center right away.

INACTIVE INGREDIENT

WATER, BUTYLENE GLYCOL, DICAPRYLYL CARBONATE, CYCLOPENTASILOXANE, DIPROPYLENE GLYCOL, PROPANEDIOL, DIMETHICONE, BIS-ETHYLHEXYLOXYPHENOL METHOXYPHENYL TRIAZINE, NIACINAMIDE, DIETHYLAMINO HYDROXYBENZOYL HEXYL BENZOATE, POLYMETHYL METHACRYLATE, HYDROGENATED POLY(C6-14 OLEFIN), POTASSIUM CETYL PHOSPHATE, C14-22 ALCOHOLS, TREHALOSE, C12-15 ALKYL BENZOATE, CETEARYL ALCOHOL, PEG-100 STEARATE, BEHENYL ALCOHOL, PHENOXYETHANOL, FRAGRANCE, C12-20 ALKYL GLUCOSIDE, ALUMINUM HYDROXIDE, POLYGLYCERYL-6 POLYRICINOLEATE, AMMONIUM ACRYLOYLDIMETHYLTAURATE/VP COPOLYMER, POLYHYDROXYSTEARIC ACID, STEARIC ACID, ACRYLATES/C10-30 ALKYL ACRYLATE CROSSPOLYMER, FERRIC OXIDE YELLOW (CI 77492), XANTHAN GUM, NEOPENTYL GLYCOL DIETHYLHEXANOATE, CAPRYLIC/CAPRIC TRIGLYCERIDE, ADENOSINE, POTASSIUM HYDROXIDE, ETHYLHEXYLGLYCERIN, FERRIC OXIDE RED (CI 77491), DISODIUM EDTA, ZINC OXIDE, TRIETHOXYCAPRYLYLSILANE, SODIUM HYALURONATE, CAMELLIA JAPONICA SEED OIL, D&C RED NO. 33 (CI 17200), NELUMBO NUCIFERA FLOWER EXTRACT, LONICERA JAPONICA (HONEYSUCKLE) FLOWER EXTRACT, SOPHORA JAPONICA FLOWER EXTRACT, CARTHAMUS TINCTORIUS (SAFFLOWER) FLOWER EXTRACT, CAMELLIA JAPONICA FLOWER EXTRACT, PRUNUS MUME FLOWER EXTRACT, PYRUS COMMUNIS (PEAR) FLOWER EXTRACT